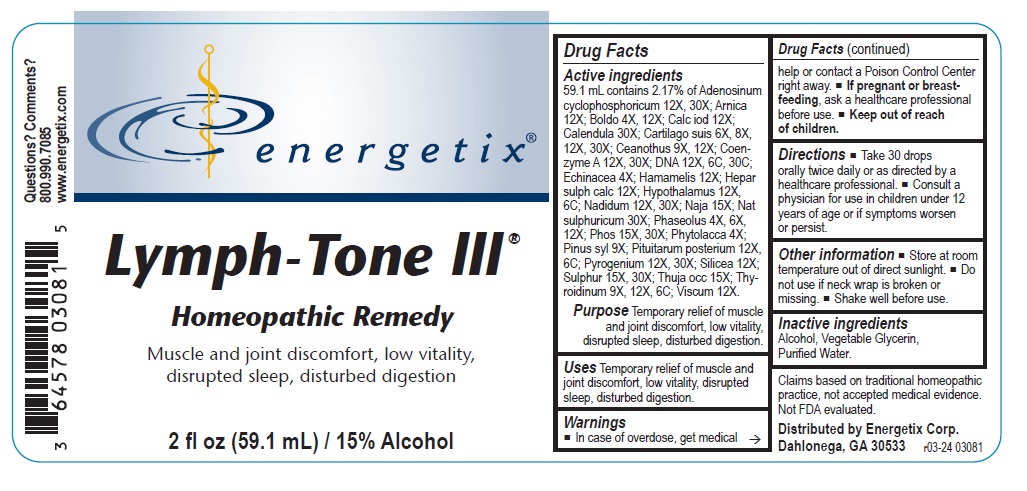 DRUG LABEL: Lymph-Tone III
NDC: 64578-0172 | Form: LIQUID
Manufacturer: Energetix Corporation
Category: homeopathic | Type: HUMAN OTC DRUG LABEL
Date: 20241120

ACTIVE INGREDIENTS: ADENOSINE CYCLIC PHOSPHATE 12 [hp_X]/59.1 mL; ARNICA MONTANA WHOLE 12 [hp_X]/59.1 mL; PEUMUS BOLDUS LEAF 4 [hp_X]/59.1 mL; CALCIUM IODIDE 12 [hp_X]/59.1 mL; CALENDULA OFFICINALIS FLOWERING TOP 30 [hp_X]/59.1 mL; SUS SCROFA CARTILAGE 6 [hp_X]/59.1 mL; CEANOTHUS AMERICANUS LEAF 9 [hp_X]/59.1 mL; COENZYME A 12 [hp_X]/59.1 mL; HERRING SPERM DNA 12 [hp_X]/59.1 mL; ECHINACEA ANGUSTIFOLIA 4 [hp_X]/59.1 mL; HAMAMELIS VIRGINIANA ROOT BARK/STEM BARK 12 [hp_X]/59.1 mL; CALCIUM SULFIDE 12 [hp_X]/59.1 mL; BOS TAURUS HYPOTHALAMUS 12 [hp_X]/59.1 mL; NADIDE 12 [hp_X]/59.1 mL; NAJA NAJA VENOM 15 [hp_X]/59.1 mL; SODIUM SULFATE 30 [hp_X]/59.1 mL; KIDNEY BEAN 4 [hp_X]/59.1 mL; PHOSPHORUS 15 [hp_X]/59.1 mL; PHYTOLACCA AMERICANA ROOT 4 [hp_X]/59.1 mL; PINUS SYLVESTRIS LEAFY TWIG 9 [hp_X]/59.1 mL; SUS SCROFA PITUITARY GLAND, POSTERIOR 12 [hp_X]/59.1 mL; RANCID BEEF 12 [hp_X]/59.1 mL; SILICON DIOXIDE 12 [hp_X]/59.1 mL; SULFUR 15 [hp_X]/59.1 mL; THUJA OCCIDENTALIS LEAFY TWIG 15 [hp_X]/59.1 mL; THYROID, UNSPECIFIED 9 [hp_X]/59.1 mL; VISCUM ALBUM FRUITING TOP 12 [hp_X]/59.1 mL
INACTIVE INGREDIENTS: ALCOHOL; GLYCERIN; WATER

Lymph-Tone III

Active ingredients

59.1 mL contains 2.17% of Adenosinum cyclophosphoricum 12X, 30X; Arnica 12X; Boldo 4X, 12X; Calc iod 12X; Calendula 30X; Cartilago suis 6X, 8X, 12X, 30X; Ceanothus 9X, 12X; Coenzyme A 12X, 30X; DNA 12X, 6C, 30C; Echinacea 4X; Hamamelis 12X; Hepar sulph calc 12X; Hypothalamus 12X, 6C; Nadidum 12X, 30X; Naja 15X; Nat sulphuricum 30X; Phaseolus 4X, 6X, 12X; Phos 15X, 30X; Phytolacca 4X;
Pinus syl 9X; Pituitarum posterium 12X, 6C; Pyrogenium 12X, 30X; Silicea 12X; Sulphur 15X, 30X; Thuja occ 15X; Thyroidinum 9X, 12X, 6C; Viscum 12X.

Claims based on traditional homeopathic practice, not accepted medical evidence. Not FDA evaluated.

INDICATIONS AND USAGE

UsesTemporary relief of muscle and joint discomfort, low vitality, disrupted sleep, disturbed digestion.

Warnings

- In case of overdose, get medical help or contact a Poison Control Center right away.
- If pregnant or breast-feeding, ask a healthcare professional before use.

- Keep out of reach of children

Directions

- Take 30 drops orally twice daily or as directed by a healthcare professional.
- Consult a physician for use in children under 12 years of age or if symptoms worsen or persist.

Other information

- Store at room temperature out of direct sunlight.
- Do not use if neck wrap is broken or missing.
- Shake well before use.

Inactive ingredients
Alcohol, Vegetable Glycerin, Purifed Water.

QUESTIONS

Distributed by Energetix Corp.

Dahlonega, GA 30533

Questions? Comments?

800.990.7085

www.energetix.com

PACKAGE LABEL

energetix

Lymph-Tone III

Homeopathic Remedy

Muscle and Joint discomfort, low vitality,

disrupted sleep, disturbed digestion.

2 fl oz (59.1 mL) / 15% Alcohol

PURPOSE

Purpose Temporary relief of muscle and joint discomfort, low vitality, disrupted sleep, disturbed digestion.